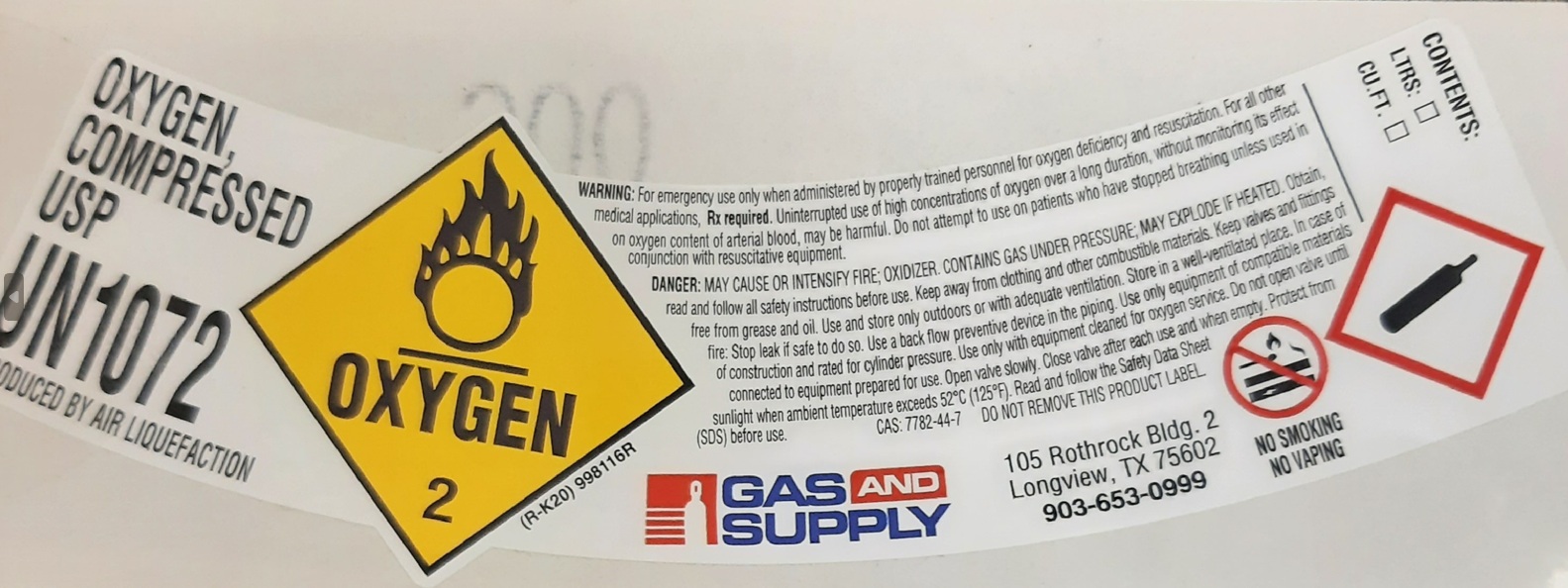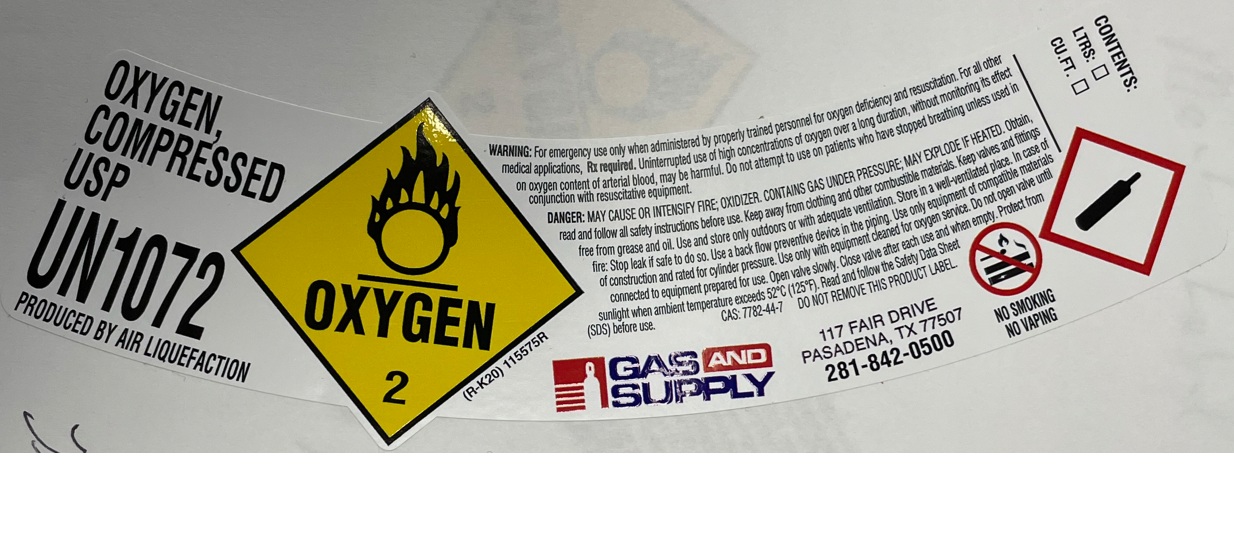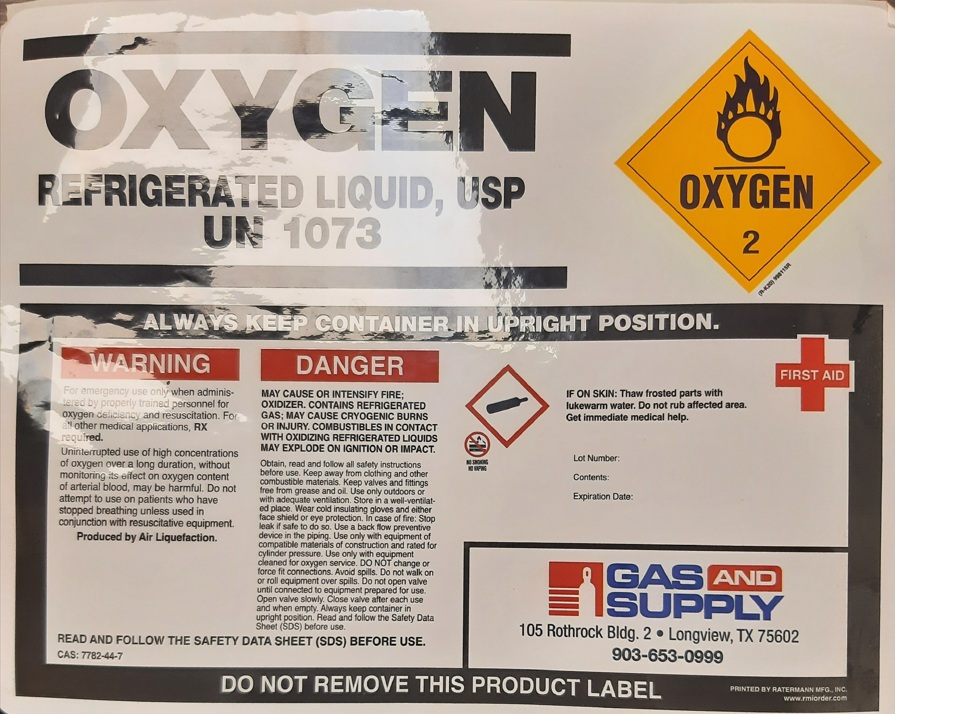 DRUG LABEL: Oxygen
NDC: 53425-001 | Form: GAS
Manufacturer: IWS Gas and Supply of Texas, LTD
Category: prescription | Type: HUMAN PRESCRIPTION DRUG LABEL
Date: 20251208

ACTIVE INGREDIENTS: OXYGEN 995 mL/1 L

Oxygen

PACKAGE LABEL

OXYGEN, COMPRESSED USP

UN1072

PRODUCED BY AIR LIQUEFACTION

WARNING: For emergency use only when administered by properly trained personnel oxygen deficiency and resuscitation. For all other medical applications, Rx required. Uninterrupted use of high concentrations of oxygen over a long duration, without monitoring its effect on oxygen content of arterial blood, may be harmful. Do not attempt to use on patients who have stopped breathing unless used in conjunction with resuscitative equipment.

DANGER: MAY CAUSE OR INTENSIFY FIRE; OXIDIZER. CONTAINS GAS UNDER PRESSURE; MAY EXPLODE IF HEATED. Obtain, read and follow all safety instructions before use. Keep away from clothing and other combustible materials. Keep valves and fittings free from grease and oil. Use and store only outdoors or with adequate ventilation. Store in a well-ventilated place. In case of fire: Stop leak if safe to do so. Use a back flow preventive device in the piping. Use only equipment of compatible materials of construction and rated for cylinder pressure. Use only with equipment cleaned for oxygen service. Do not open valve until connected to equipment prepared for use. Open valve slowly. Close valve after each use and when empty. Protect from sunlight when ambient temperature exceeds 52 C (125 F). Read and follow the Safety Data Sheet (SDS) before use.

CAS: 7782-44-7 DO NOT REMOVE THIS PRODUCT LABEL.

GAS AND SUPPLY

105 Rothrock Bldg. 2

Longview, TX 75602

903-653-0999

NO SMOKING

NO VAPING

CONTENTS: LTRS: CU.FT.

PACKAGE LABEL

OXYGEN, COMPRESSED USP

UN1072

PRODUCED BY AIR LIQUEFACTION

WARNING: For emergency use only when administered by properly trained personnel for oxygen deficiency and resuscitation. For all other medical applications, Rx required. Uninterrupted use of high concentrations of oxygen over a long duration, without monitoring its effect on oxygen content of arterial blood, may be harmful. Do not attempt to use on patients who have stopped breathing unless used in conjunction with resuscitative equipment.

DANGER: MAY CAUSE OR INTENSIFY FIRE; OXIDIZER. CONTAINS GAS UNDER PRESSURE; MAY EXPLODE IF HEATED. Obtain, read and follow all safety instructions before use. Keep away from clothing and other combustible materials. Keep valves and fittings free from grease and oil. Use and store only outdoors or with adequate ventilation. Store in a well-ventilated place. In case of fire: Stop leak if safe to do so. Use a back flow preventive device in the piping. Use only equipment of compatible materials of construction and rated for cylinder pressure. Use only with equipment cleaned for oxygen service. Do not open valve until connected to equipment prepared for use. Open valve slowly. Close valve after each use when empty. Protect from sunlight when ambient temperature exceeds 52 C (125 F). Read and follow the Safety Data Sheet (SDS) before use.

CAS: 7782-44-7 DO NOT REMOVE THIS PRODUCT LABEL.

GAS AND SUPPLY

117 FAIR DRIVE

PASADENA, TX 77507

281-842-0500

NO SMOKING

NO VAPING

CONTENTS: LTRS: CU.FT.

PACKAGE LABEL

OXYGEN

REFRIGERATED LIQUID, USP

UN 1073

ALWAYS KEEP CONTAINER IN UPRIGHT POSITION.

WARNING

For emergency use only when administered by properly trained personnel for oxygen deficiency and resuscitation. For all other medical applications, Rx required.

Uninterrupted use of high concentrations of oxygen over a long duration, without monitoring its effect on oxygen content of arterial blood, may be harmful. Do not attempt to use on patients who have stopped breathing unless used in conjunction with resuscitative equipment.

Produced by Air Liquefaction.

DANGER

MAY CAUSE OR INTENSIFY FIRE; OXIDIZIER. CONTAINS REFRIGERATED GAS; MAY CAUSE CRYOGENIC BURNS OR INJURY. COMBUSTIBLES IN CONTACT WITH OXIDIZING REFRIGERATED LIQUIDS MAY EXPLODE ON IGNITION OR IMPACT.

Obtain, read and follow all safety instructions before use. Keep away from clothing and other combustible materials. Keep valves and fittings free from grease and oil. Use only outdoors or with adequate ventilation. Store in a well-ventilated place. Wear cold insulating gloves and either face shield or eye protection. In case of fire: Stop leak if safe to do so. Use a back flow preventive device in the piping. Use only with equipment of compatible materials of construction and rated for cylinder pressure. Use only with equipment cleaned for oxygen service. DO NOT change or force fit connections. Avoid spills. Do not walk on or roll equipment over spills. Do not open valve until connected to equipment prepared for use. Open valve slowly. Close valve after each use and when empty. Always keep container in upright position. Read and follow the Safety Data Sheet (SDS) before use.

READ AND FOLLOW THE SAFETY DATA SHEET (SDS) BEFORE USE.

CAS: 7782-44-7

NO SMOKING

NO VAPING

FIRST AID IF ON SKIN: Thaw frosted parts with lukewarm water. Do not rub affected area. Get immediate medical help.

Lot Number:

Contents:

Expiration Date:

GAS AND SUPPLY

105 Rothrock Bldg. 2

Longview, TX 75602

903-653-0999

DO NOT REMOVE THIS PRODUCT LABEL